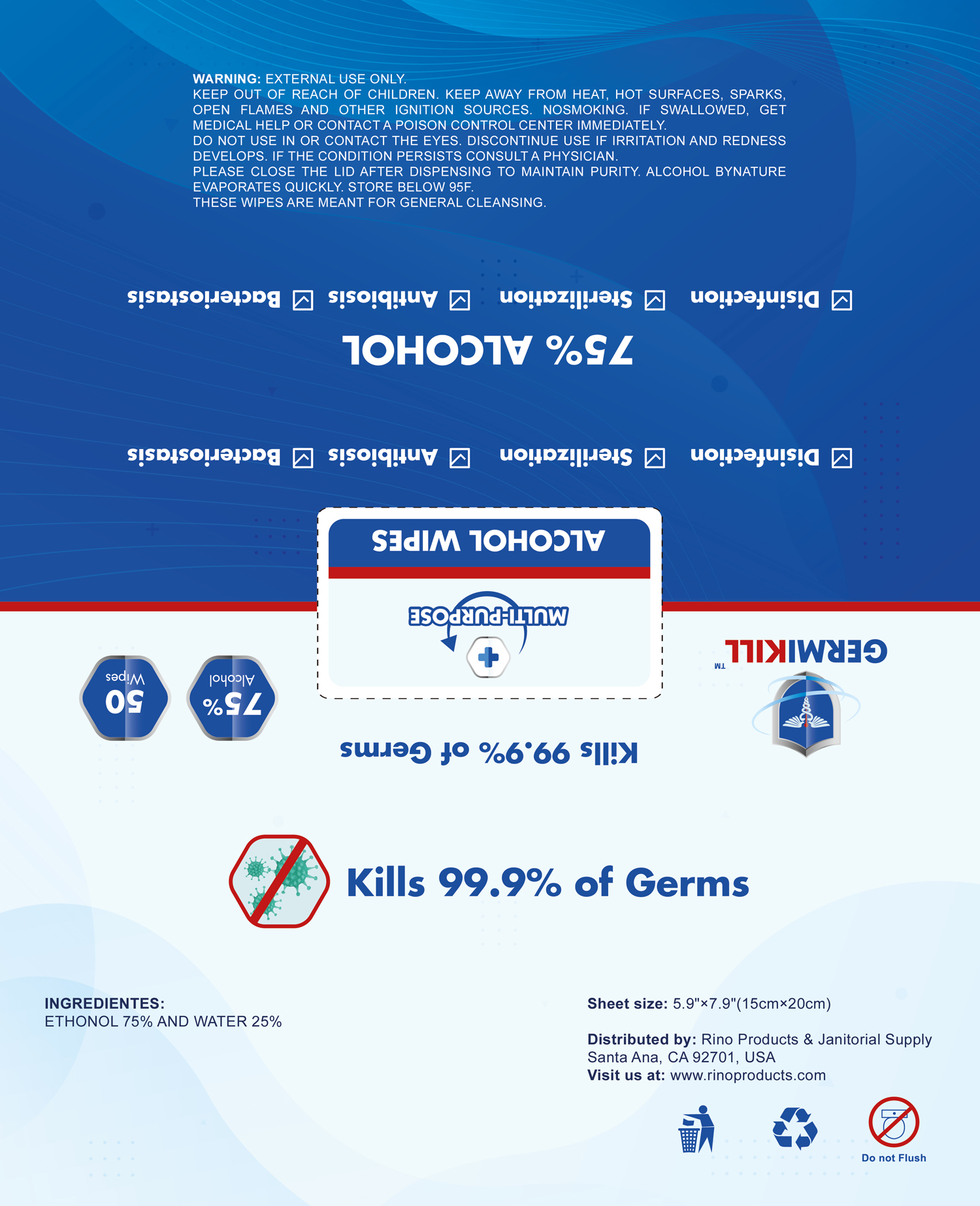 DRUG LABEL: ALCOHOL WIPES
NDC: 75662-002 | Form: CLOTH
Manufacturer: Ningbo Chenxing Daily Necessities Co., Ltd.
Category: otc | Type: HUMAN OTC DRUG LABEL
Date: 20200623

ACTIVE INGREDIENTS: ALCOHOL 0.75 mL/1 g
INACTIVE INGREDIENTS: WATER; CHLORHEXIDINE GLUCONATE

ALCOHOL WIPES

Active Ingredient(s)

Alcohol 75%. Purpose: Antiseptic

Purpose

Antiseptic, Wet Wipes

Use

Disinfection

Sterilization

Antibiosis

Bacteriostasis

Warnings

External use only.

Keep away from heat, hot surface, sparks, open flames, and other igition sources. Nonsmoking.

Keep out of reach of children. If swallowed, get medical help or contact a poison control center immediately.

Do not use

in or contact the eyes.

WHEN USING

Avoid direct contact with eyes. In case of eye contact, flush eyes with water.

STOP USE

Discontunue use if irritation and redness develops. If the condition persists consult a physician.

Directions

These wipes are meant for general cleansing

Other information

Please close the lid after dispensing to maintain purity. Alcohol by nature evaporates quickly. Store below 95F.

Inactive ingredients

water

Package Label - Principal Display Panel

75662-002-01 50 wipes